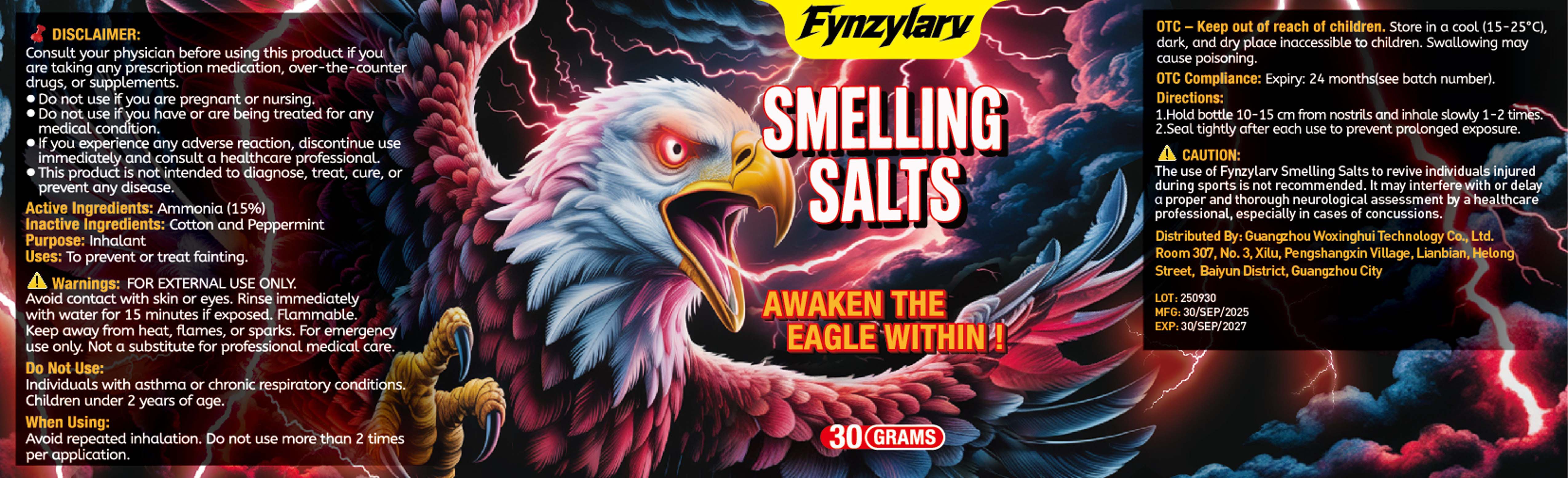 DRUG LABEL: Smelling Salt
NDC: 87175-001 | Form: INHALANT
Manufacturer: Guangzhou Woxinghui Technology Co., Ltd.
Category: otc | Type: HUMAN OTC DRUG LABEL
Date: 20251022

ACTIVE INGREDIENTS: AMMONIUM CARBONATE 4.5 g/30 g
INACTIVE INGREDIENTS: PEPPERMINT; COTTON

87175-001 Smelling Salt

ACTIVE INGREDIENT

Ammonium Carbonate

PURPOSE

Inhalant

INDICATIONS AND USAGE

To prevent or treat fainting.

WARNINGS

FOR EXTERNAL USE ONLY.
Avoid contact with skin or eyes. Rinse immediatelywith water for 15 minutes if exposed. Flammable.Keep away from heat, flames, or sparks. For emergency
use only. Not a substitute for professional medical care.

DO NOT USE

Individuals with asthma or chronic respiratory conditions.
Children under 2 years of age.

WHEN USING

Avoid repeated inhalation. Do not use more than 2 times
per application.

If you experience any adverse reaction, discontinue use
immediately and consult a healthcare professional.

KEEP OUT OF REACH OF CHILDREN

0TC- Keep out of reach of children, Store in a cool(15-25°C)
dark, and dry place inaccessible to children. Swallowing may
cause poisoning.

DOSAGE AND ADMINISTRATION

1.Hold bottle 10-15 am from nostrils and inhale slowly 1-2 times.
2.Seal tightly after each use to prevent prolonged exposure.

INACTIVE INGREDIENT

Cotton
Peppermint Flavour